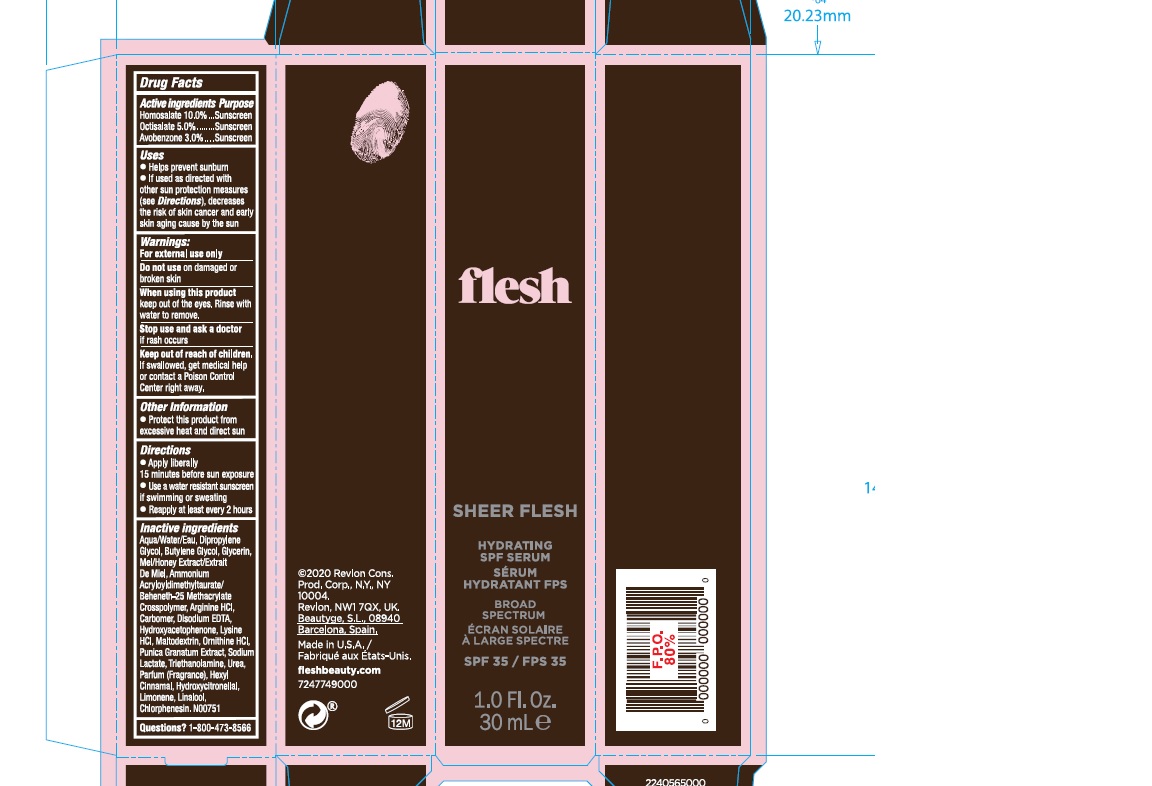 DRUG LABEL: Flesh Hydrating SPF Serum
NDC: 10967-660 | Form: LOTION
Manufacturer: Revlon Consumer Products Corporation
Category: otc | Type: HUMAN OTC DRUG LABEL
Date: 20200401

ACTIVE INGREDIENTS: HOMOSALATE 10 mg/1 mL; OCTISALATE 5 mg/1 mL; AVOBENZONE 3 mg/1 mL
INACTIVE INGREDIENTS: BUTYLENE GLYCOL; GLYCERIN; HONEY; AMMONIUM ACRYLOYLDIMETHYLTAURATE/BEHENETH-25 METHACRYLATE CROSSPOLYMER (52000 MPA.S); CARBOMER HOMOPOLYMER, UNSPECIFIED TYPE; UREA; HYDROXYCITRONELLAL; LINALOOL, (+)-; PUNICA GRANATUM ROOT BARK; SODIUM LACTATE; ORNITHINE HYDROCHLORIDE; TROLAMINE; .ALPHA.-HEXYLCINNAMALDEHYDE; LIMONENE, (+)-; WATER; ARGININE HYDROCHLORIDE; EDETATE DISODIUM ANHYDROUS; HYDROXYACETOPHENONE; DIPROPYLENE GLYCOL; LYSINE HYDROCHLORIDE; MALTODEXTRIN; CHLORPHENESIN

Flesh Hydrating SPF Serum

Drug Facts

Avobenzone 3.0%

Homosalate 10.0%

Octisalate 5.0%

Purpose

Sunscreen

Uses

- Helps prevent submburn

- If used as directed with other sun protection measures (see Directions), decreases the risk of skin cancerand early skin aging caused by the sun.

Warnings

- For external use only

- Do not use on danaged or broken skin

- When using this product keep out of eyes. Rinse with water to remove.

- Stop use and ask a doctor if rash occurs

- Keep out of reach of children. If swallowed get medical helpor contact a Poison Control Center right away.

Directions

- Apply liberally 15 minutes before sun exposure

- Use a water resistant sunscreen if swimming or sweating

- Reapply at least every 2 hours

Other Information

Protect this product from excessive heat and direct sun